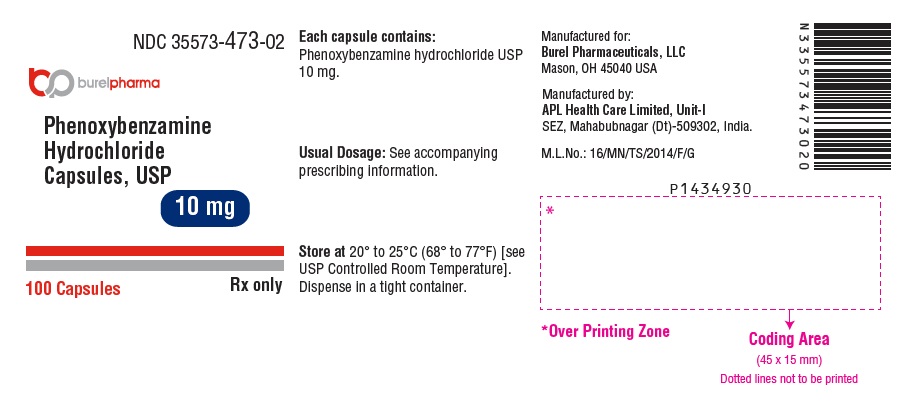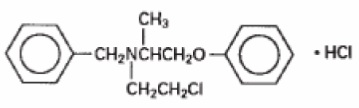 DRUG LABEL: PHENOXYBENZAMINE HYDROCHLORIDE
NDC: 35573-473 | Form: CAPSULE
Manufacturer: Burel Pharmaceuticals, LLC
Category: prescription | Type: Human Prescription Drug Label
Date: 20240809

ACTIVE INGREDIENTS: PHENOXYBENZAMINE HYDROCHLORIDE 10 mg/1 1
INACTIVE INGREDIENTS: ANHYDROUS LACTOSE; TALC; GELATIN, UNSPECIFIED; TITANIUM DIOXIDE; FERROSOFERRIC OXIDE; POTASSIUM HYDROXIDE; PROPYLENE GLYCOL; SHELLAC

Phenoxybenzamine Hydrochloride Capsules, USP 10 mg
adrenergic, alpha-receptor-blocking agent
Rx only

DESCRIPTION

Each phenoxybenzamine hydrochloride capsule, USP with white opaque cap and body, is imprinted "PHEH" on cap and "10" on body, and contains 10 mg of phenoxybenzamine hydrochloride USP. Inactive ingredients consist of anhydrous lactose and talc. The capsule shell contains gelatin and titanium dioxide.
The imprinting ink contains black iron oxide, potassium hydroxide, propylene glycol, and shellac.

Phenoxybenzamine hydrochloride is N-(2-Chloroethyl)-N-(1-methyl-2-phenoxyethyl)benzylamine hydrochloride:

Phenoxybenzamine hydrochloride USP is white or almost white crystalline powder with a molecular weight of 340.3, which melts between 136° and 141°C. It is freely soluble in ethanol, sparingly soluble in water.

CLINICAL PHARMACOLOGY

Phenoxybenzamine hydrochloride is a long-acting, adrenergic, alpha-receptor-blocking agent, which can produce and maintain “chemical sympathectomy” by oral administration. It increases blood flow to the skin, mucosa and abdominal viscera, and lowers both supine and erect blood pressures. It has no effect on the parasympathetic system.

Twenty to 30 percent of orally administered phenoxybenzamine appears to be absorbed in the active form.^1

The half-life of orally administered phenoxybenzamine hydrochloride is not known; however, the half-life of intravenously administered drug is approximately 24 hours. Demonstrable effects with intravenous administration persist for at least 3 to 4 days, and the effects of daily administration are cumulative for nearly a week.^1

INDICATION AND USAGE

Phenoxybenzamine hydrochloride capsules are indicated in the treatment of pheochromocytoma, to control episodes of hypertension and sweating. If tachycardia is excessive, it may be necessary to use a beta-blocking agent concomitantly.

CONTRAINDICATIONS

Conditions where a fall in blood pressure may be undesirable; hypersensitivity to the drug or any of its components.

WARNING

Phenoxybenzamine hydrochloride-induced alpha-adrenergic blockade leaves beta-adrenergic receptors unopposed. Compounds that stimulate both types of receptors may, therefore, produce an exaggerated hypotensive response and tachycardia.

PRECAUTIONS

General–Administer with caution in patients with marked cerebral or coronary arteriosclerosis or renal damage. Adrenergic blocking effect may aggravate symptoms of respiratory infections.

Drug Interactions^2 – Phenoxybenzamine hydrochloride may interact with compounds that stimulate both alpha- and beta-adrenergic receptors (i.e., epinephrine) to produce an exaggerated hypotensive response and tachycardia. (See WARNING.)

Phenoxybenzamine hydrochloride blocks hyperthermia production by levarterenol, and blocks hypothermia production by reserpine.

Carcinogenesis and Mutagenesis

Case reports of carcinoma in humans after long-term treatment with phenoxybenzamine have been reported. Hence long-term use of phenoxybenzamine is not recommended.^(3, 4) Carefully weigh the benefits and risks before prescribing this drug.

Phenoxybenzamine hydrochloride showed in vitro mutagenic activity in the Ames test and mouse lymphoma assay; it did not show mutagenic activity in vivo in the micronucleus test in mice. In rats and mice, repeated intraperitoneal administration of phenoxybenzamine hydrochloride (three times per week for up to 52 weeks) resulted in peritoneal sarcomas. Chronic oral dosing in rats (for up to 2 years) produced malignant tumors of the small intestine and non-glandular stomach, as well as ulcerative and/or erosive gastritis of the glandular stomach. Whereas squamous cell carcinomas of the non-glandular stomach were observed at all tested doses of phenoxybenzamine hydrochloride, there was a no-observed-effect-level of 10 mg/kg for tumors (carcinomas and sarcomas) of the small intestine. This dose is, on a body surface area basis, about twice the maximum recommended human dosage of 20 mg b.i.d.

Pregnancy - Teratogenic Effects

Adequate reproductive studies in animals have not been performed with phenoxybenzamine hydrochloride. It is also not known whether phenoxybenzamine hydrochloride can cause fetal harm when administered to a pregnant woman. Phenoxybenzamine hydrochloride should be given to a pregnant woman only if clearly needed.

Nursing Mothers

It is not known whether this drug is excreted in human milk. Because many drugs are excreted in human milk, and because of the potential for serious adverse reactions from phenoxybenzamine hydrochloride, a decision should be made whether to discontinue nursing or to discontinue the drug, taking into account the importance of the drug to the mother.

Pediatric Use

Safety and effectiveness in pediatric patients have not been established.

ADVERSE REACTIONS

The following adverse reactions have been observed, but there are insufficient data to support an estimate of their frequency.

Autonomic Nervous System*: Postural hypotension, tachycardia, inhibition of ejaculation, nasal congestion, miosis.

*These so-called “side effects” are actually evidence of adrenergic blockade and vary according to the degree of blockade.

Miscellaneous: Gastrointestinal irritation, drowsiness, fatigue.
To report SUSPECTED ADVERSE REACTIONS, contact Aurobindo Pharma USA, Inc. at 1-866-850-2876 or FDA at 1-800-FDA-1088 or www.fda.gov/medwatch.

OVERDOSAGE

SYMPTOMS - These are largely the result of blocking of the sympathetic nervous system and of the circulating epinephrine. They may include postural hypotension, resulting in dizziness or fainting; tachycardia, particularly postural; vomiting; lethargy; shock.

TREATMENT

When symptoms and signs of overdosage exist, discontinue the drug. Treatment of circulatory failure, if present, is a prime consideration. In cases of mild overdosage, recumbent position with legs elevated usually restores cerebral circulation. In the more severe cases, the usual measures to combat shock should be instituted. Usual pressor agents are not effective. Epinephrine is contraindicated because it stimulates both alpha- and beta- receptors; since alpha- receptors are blocked, the net effect of epinephrine administration is vasodilation and a further drop in blood pressure (epinephrine reversal).

The patient may have to be kept flat for 24 hours or more in the case of overdose, as the effect of the drug is prolonged. Leg bandages and an abdominal binder may shorten the period of disability.

I.V. Infusion of levarterenol bitartrate** may be used to combat severe hypotensive reactions, because it stimulates alpha- receptors primarily. Although phenoxybenzamine hydrochloride is an alpha-adrenergic blocking agent, a sufficient dose of levarterenol bitartrate will overcome this effect.

The oral LD50 for phenoxybenzamine hydrochloride is approximately 2000 mg/kg in rats and approximately 500 mg/kg in guinea pigs.

DOSAGE AND ADMINISTRATION

The dosage should be adjusted to fit the needs of each patient. Small initial doses should be slowly increased until the desired effect is obtained or the side effects from blockade become troublesome. After each increase, the patient should be observed on that level before instituting another increase. The dosage should be carried to a point where symptomatic relief and/or objective improvement are obtained, but not so high that the side effects from blockade become troublesome.

Initially, 10 mg of phenoxybenzamine hydrochloride twice a day. Dosage should be increased every other day, usually to 20 to 40 mg 2 or 3 times a day, until an optimal dosage is obtained, as judged by blood pressure control.

Long-term use of phenoxybenzamine is not recommended (see PRECAUTIONS Carcinogenesis and Mutagenesis).

STORAGE

Store at 20° to 25°C (68° to 77°F) [see USP Controlled Room Temperature]. Dispense in a tight container.

HOW SUPPLIED

Phenoxybenzamine Hydrochloride Capsules USP, 10 mg are white opaque colored cap and white opaque colored body hard gelatin capsules, imprinted with “PHEH” on cap and “10” on body, filled with white to off-white powder.

Bottle of 100 NDC 35573-473-02

REFERENCES

1. Weiner, N.: Drugs That Inhibit Adrenergic Nerves and Block Adrenergic Receptors, in Goodman, L., and Gilman, A., The Pharmacological Basis of Therapeutics, ed. 6, New York, Macmillan Publishing Co., 1980, p. 179; p. 182.

2. Martin, E.W.: Drug Interactions Index 1978/1979, Philadelphia, J.B. Lippincott Co., 1978, pp. 209-210.

3. Nettesheim O, Hoffken G, Gahr M, Breidert M: Haematemesis and dysphagia in a 20-year-old woman with congenital spine malformation and situs inversus partialis [German]. Zeitschrift fur Gastroenterologie. 2003;41(4):319-24.

4. Vaidyanathan S, Mansour P, Soni BM, Hughes PL, Singh G: Chronic lymphocytic leukaemia, synchronous small cell carcinoma and squamous neoplasia of the urinary bladder in a paraplegic man following long-term phenoxybenzamine therapy. Spinal Cord. 2006;44(3):188-91.

** Available as Levophed® Bitartrate (brand of norepinephrine bitartrate) from Abbott Laboratories.
Manufactured for:
Burel Pharmaceuticals, LLC
Mason, OH 45040 USA
Manufactured by:
APL Health Care Limited, Unit-I
SEZ, Mahabubnagar (Dt)-509302, India.
M.L.No.: 16/MN/TS/2014/F/G
Issued: July 2024

PACKAGE LABEL-PRINCIPAL DISPLAY PANEL - 10 mg (100 Capsules Bottle)

NDC 35573-473-02
burel pharma
Phenoxybenzamine
Hydrochloride
Capsules, USP
10 mg
100 Capsules Rx only